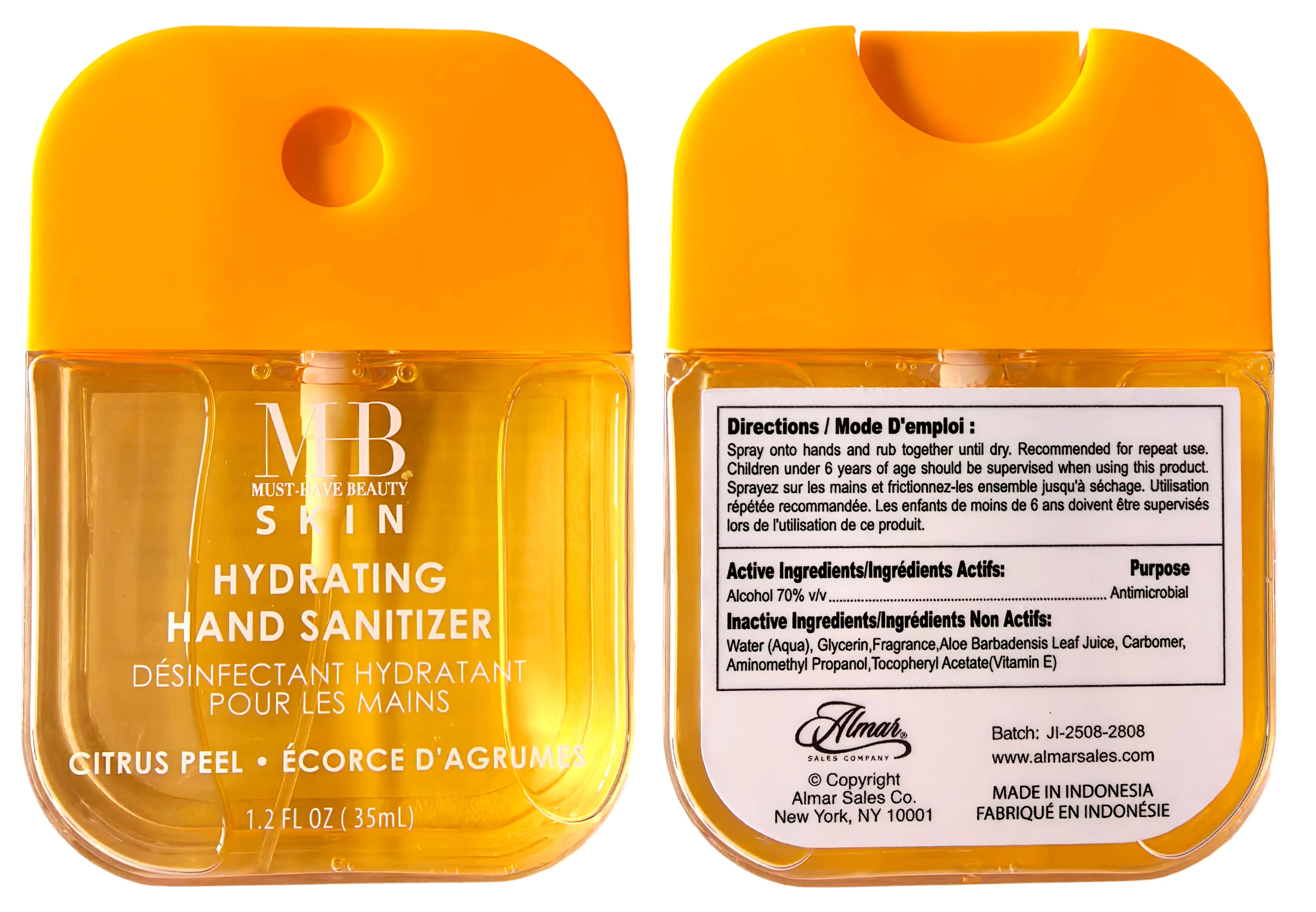 DRUG LABEL: MHB SKIN HYDRATING HAND SANITIZER, CITRUS PEEL
NDC: 85537-117 | Form: SPRAY
Manufacturer: PT SUPER HOME PRODUCT INDONESIA
Category: otc | Type: HUMAN OTC DRUG LABEL
Date: 20260115

ACTIVE INGREDIENTS: ALCOHOL 70 mL/100 mL
INACTIVE INGREDIENTS: CARBOMER; CI 15985; AQUA; ALOE VERA LEAF JUICE; CI 19140; AMINOMETHYL PROPANOL; GLYCERIN; ALPHA-TOCOPHEROL ACETATE; FRAGRANCE 13576

MHB SKIN HYDRATING HAND SANITIZER, CITRUS PEEL 35ml

Directions:

Spray onto hands and rub together untl dry. Recommended for repeat use.Children under 6 years of age should be supervised when using this product.

Inactive Ingredients:

Water (Aqua),Glycerin,Fragrance,Tocopheryl Acetate (Vitamin E),Carbomer,Aloe Barbadensis Leaf Juice,Aminomethyl Propanol,CI15985, CI19140

Warnings

For external use only, Flammable, keep away from fire or flame.

When using this product:

In case of contact with eyes, rinse eyes thoroughly with water. Avoid contact with broken skin.

Stop use and ask a doctor if:

Irritation and redness occurs.

Keep out of reach of children:

If swallowed, get medical help or contact a Poison Control Center

Active Ingredients:

Ethyl Alcohol 70% v/v Purpose: Antimicrobial.

Use:

Hand sanitizer helps reduce bacteria and the spread of germs.